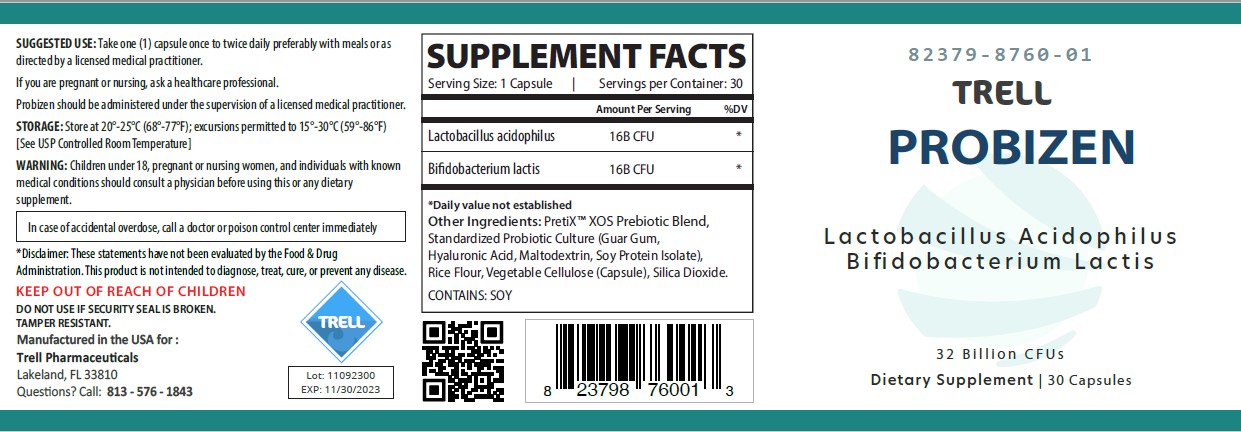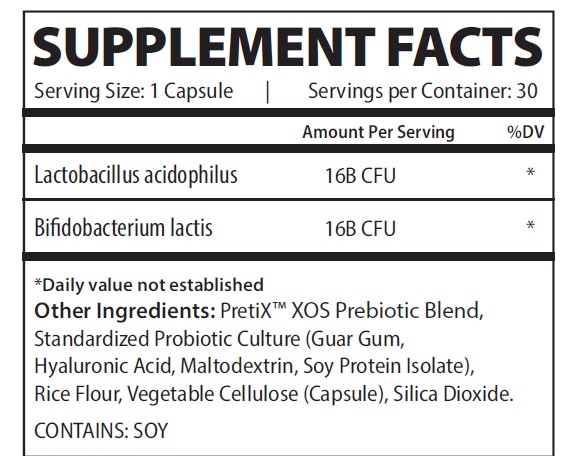 DRUG LABEL: Probizen
NDC: 82379-8760 | Form: CAPSULE
Manufacturer: Trell Pharma
Category: other | Type: DIETARY SUPPLEMENT
Date: 20220825

ACTIVE INGREDIENTS: LACTOBACILLUS ACIDOPHILUS 16000000000 [CFU]/1 1; BIFIDOBACTERIUM ANIMALIS LACTIS 16000000000 [CFU]/1 1

Probizen

STATEMENT OF IDENTITY

Probizen

Other Ingredients: PretiX Prebiotic Blend, Standardized Probiotic Culture (Guar Gum, Hyaluronic Acid, Maltodextrin, Soy Protein Isolate), Rice Flour, Vegetable Cellulose (Capsule), Silica Dioxide
Probizen is an orally administered prescription probiotic formulation for the clinical dietary management of suboptimal nutritional status in patients where advanced supplementation is required and nutritional supplementation in physiologically stressful conditions for maintenance of good health is needed.
Probizen should be administered under the supervision of a licensed medical practitioner.
Probizen is manufactured in accordance with Current Good Manufacturing Practice for foods, using ingredients that have been approved by the U.S. Food and Drug Administration (FDA) as food additives or are Generally Recognized as Safe (GRAS) for their intended use.

DOSAGE

Take one (1) capsule once to twice daily preferably with meals or as directed by medical practitioner.

If you are pregnant or nursing, ask a healthcare professional.

Probizen should be administered under the supervision of a licensed medical practitioner.

SAFE HANDLING

This product is contraindicated in patients with a known hypersensitivity to any of the ingredients.

Probizen should only be used under the direction and supervision of a licensed medical practitioner.

WARNING: Children under 18, pregnant or nursing women, and individuals with known medical conditions should consult a physician before using this or any dietary supplement.

In case of accidental overdoes, call a doctor or poison control center immediately.

KEEP OUT OF REACH OF CHILDREN

STORAGE

Store at 20°-25°C (68°-77°F); excursions permitted to 15°-30°C (59°-86°F).

HOW SUPPLIED HEALTH CLAIM

Probizen Probiotic Capsule

Dietary Supplement

NHRIC: 82379-8760-1 *

Bottles contain 30 Capsules

Distributed in the USA by:
Trell Pharma, LLC

*Does not represent these product codes to be National Drug Codes (NDC). Product codes are formatted according to standard industry practice, to meet the formatting requirement by pedigree reporting and supply-chain control including pharmacies.

† The most appropriate way to ensure pedigree reporting consistent with these regulatory guidelines and safety monitoring is to dispense this product by prescription. This is not an Orange Book product. This product may be administered only under a physician’s supervision and all prescriptions using this product shall be pursuant to state statutes as applicable. The ingredients, indication or claims of this product are not to be construed to be drug claims.